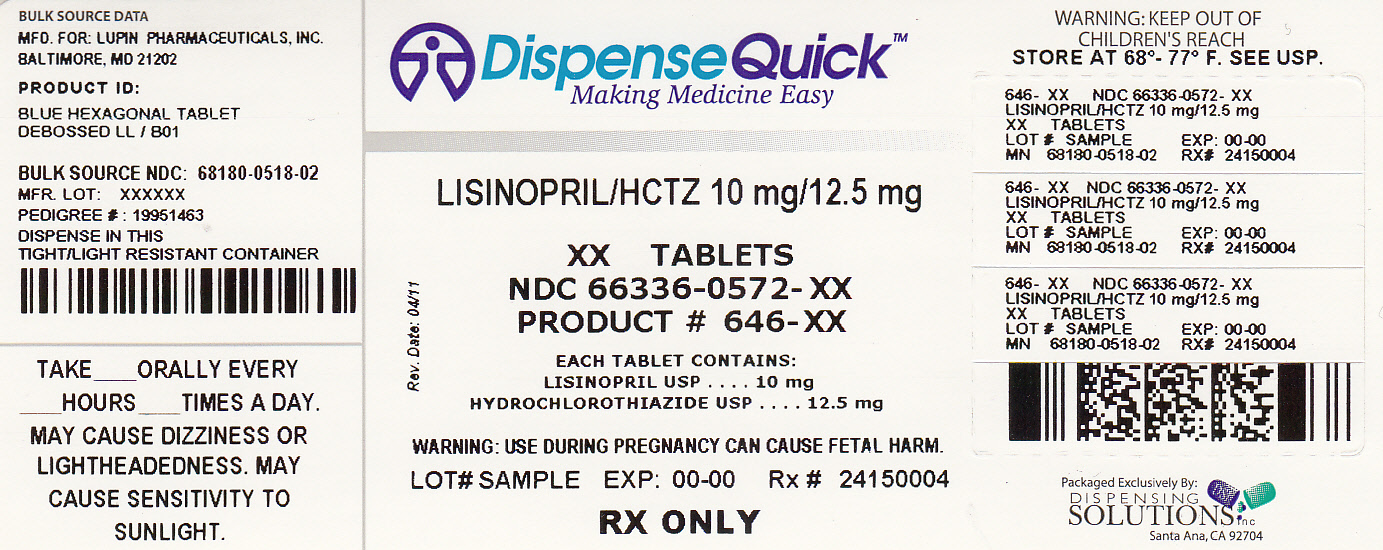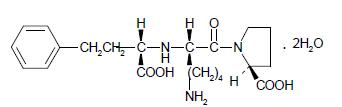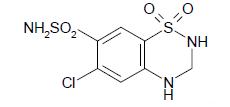 DRUG LABEL: LISINOPRIL AND HYDROCHLOROTHIAZIDE
NDC: 66336-572 | Form: TABLET
Manufacturer: Dispensing Solutions, Inc.
Category: prescription | Type: HUMAN PRESCRIPTION DRUG LABEL
Date: 20111107

ACTIVE INGREDIENTS: HYDROCHLOROTHIAZIDE 12.5 mg/1 1; LISINOPRIL 10 mg/1 1
INACTIVE INGREDIENTS: ANHYDROUS DIBASIC CALCIUM PHOSPHATE; FD&C BLUE NO. 2; MANNITOL; STARCH, CORN; MAGNESIUM STEARATE; STARCH, PREGELATINIZED CORN

LISINOPRIL AND HYDROCHLOROTHIAZIDE USP

10 mg/12.5 mg, 20 mg/12.5 mg and 20 mg/25 mg
Rx only

BOXED WARNING

USE IN PREGNANCY
When used in pregnancy during the second and third trimesters, ACE inhibitors can cause injury and even death to the developing fetus. When pregnancy is detected, lisinopril and hydrochlorothiazide tablets should be discontinued as soon as possible. See WARNINGS, Pregnancy, Lisinopril, Fetal/Neonatal Morbidity and Mortality.

DESCRIPTION

Lisinopril and hydrochlorothiazide tablets combines an angiotensin converting enzyme inhibitor, lisinopril, and a diuretic, hydrochlorothiazide.
Lisinopril, a synthetic peptide derivative, is an oral long-acting angiotensin converting enzyme inhibitor. It is chemically described as (S)-1-[N2-(1-carboxy-3-phenylpropyl)-L-lysyl]-L-proline dihydrate. Its empirical formula is C21H31N3O5•2H2O and its structural formula is:

Lisinopril is a white to off-white, crystalline powder, with a molecular weight of 441.52. It is soluble in water, sparingly soluble in methanol, and practically insoluble in ethanol.
Hydrochlorothiazide is 6-chloro-3,4-dihydro-2H-1,2,4-benzothiadiazine-7-sulfonamide 1,1-dioxide. Its empirical formula is C7H8ClN3O4S2 and its structural formula is:

Hydrochlorothiazide is a white, or practically white, crystalline powder with a molecular weight of 297.73, which is slightly soluble in water, but freely soluble in sodium hydroxide solution.
Lisinopril and hydrochlorothiazide tablets are available for oral use in three tablet combinations of lisinopril with hydrochlorothiazide: lisinopril and hydrochlorothiazide tablets 10 mg/12.5 mg, containing 10 mg lisinopril and 12.5 mg hydrochlorothiazide, lisinopril and hydrochlorothiazide tablets 20 mg/12.5 mg, containing 20 mg lisinopril and 12.5 mg hydrochlorothiazide and lisinopril and hydrochlorothiazide tablets 20 mg/25 mg, containing 20 mg lisinopril and 25 mg hydrochlorothiazide.
Inactive ingredients are dibasic calcium phosphate, magnesium stearate, mannitol, pregelatinized starch and starch. Lisinopril and hydrochlorothiazide tablets 10 mg/12.5 mg also contains FD and C Blue No. 2 Aluminum Lake. Lisinopril and hydrochlorothiazide tablets 20 mg/12.5 mg also contains yellow iron oxide and lisinopril and hydrochlorothiazide tablets 20 mg/25 mg also contain red iron oxide.

INDICATIONS AND USAGE

Lisinopril and hydrochlorothiazide tablets are indicated for the treatment of hypertension.
These fixed-dose combinations are not indicated for initial therapy (see DOSAGE AND ADMINISTRATION).
In using lisinopril and hydrochlorothiazide tablets, consideration should be given to the fact that an angiotensin converting enzyme inhibitor, captopril, has caused agranulocytosis, particularly in patients with renal impairment or collagen vascular disease, and that available data are insufficient to show that lisinopril does not have a similar risk. (See WARNINGS.)
In considering use of lisinopril and hydrochlorothiazide tablets, it should be noted that Black patients receiving ACE inhibitors have been reported to have a higher incidence of angioedema compared to non-Blacks. (See WARNINGS, Head and Neck Angioedema.)

CONTRAINDICATIONS

Lisinopril and hydrochlorothiazide is contraindicated in patients who are hypersensitive to any component of this product and in patients with a history of angioedema related to previous treatment with an angiotensin converting enzyme inhibitor and in patients with hereditary or idiopathic angioedema. Because of the hydrochlorothiazide component, this product is contraindicated in patients with anuria or hypersensitivity to other sulfonamide-derived drugs.

ADVERSE REACTIONS

Lisinopril and hydrochlorothiazide has been evaluated for safety in 930 patients, including 100 patients treated for 50 weeks or more.
In clinical trials with lisinopril and hydrochlorothiazide no adverse experiences peculiar to this combination drug have been observed. Adverse experiences that have occurred have been limited to those that have been previously reported with lisinopril or hydrochlorothiazide.
The most frequent clinical adverse experiences in controlled trials (including open label extensions) with any combination of lisinopril and hydrochlorothiazide were: dizziness (7.5 percent), headache (5.2 percent), cough (3.9 percent), fatigue (3.7 percent) and orthostatic effects (3.2 percent), all of which were more common than in placebo-treated patients. Generally, adverse experiences were mild and transient in nature; but see WARNINGSregarding angioedema and excessive hypotension or syncope. Discontinuation of therapy due to adverse effects was required in 4.4 percent of patients, principally because of dizziness, cough, fatigue and muscle cramps.
Adverse experiences occurring in greater than one percent of patients treated with lisinopril plus hydrochlorothiazide in controlled clinical trials are shown below.

Percent of Patients in Controlled Studies

 | Lisinopril-Hydrochlorothiazide (n=930) Incidence (discontinuation) | Placebo (n=207) Incidence
Dizziness | 7.5 (.8) | 1.9
Headache | 5.2 (0.3) | 19
Cough | 3.9 (0.6) | 1.0
Fatigue | 3.7 (0.4) | 1.0
Orthostatic Effects | 3.2 (0.1) | 1.0
Diarrhea | 2.5 (0.2) | 2.4
Nausea | 2.2 (0.1) | 2.4
Upper Respiratory Infection | 2.2 (0.0) | 0.0
Muscle Cramps | 2.0 (0.4) | 0.5
Asthenia | 1.8 (0.2) | 1.0
Parasthesia | 1.5 (0.1) | 0.0
Hypotension | 1.4 (0.3) | 0.5
Vomiting | 1.4 (0.1) | 0.5
Dyspepsia | 1.3 (0.0) | 0.0
Rash | 1.2 (0.1) | 0.5
Impotence | 1.2 (0.3) | 0.0

Clinical adverse experiences occurring in 0.3 to 1.0 percent of patients in controlled trials included: Body as a Whole: Chest pain, abdominal pain, syncope, chest discomfort, fever, trauma, virus infection. Cardiovascular: Palpitation, orthostatic hypotension. Digestive: Gastrointestinal cramps, dry mouth, constipation, heartburn. Musculoskeletal: Back pain, shoulder pain, knee pain, back strain, myalgia, foot pain. Nervous/Psychiatric: Decreased libido, vertigo, depression, somnolence. Respiratory: Common cold, nasal congestion, influenza, bronchitis, pharyngeal pain, dyspnea, pulmonary congestion, chronic sinusitis, allergic rhinitis, pharyngeal discomfort. Skin: Flushing, pruritus, skin inflammation, diaphoresis. Special Senses: Blurred vision, tinnitus, otalgia. Urogenital: Urinary tract infection.
Angioedema: Angioedema has been reported in patients receiving lisinopril and hydrochlorothiazide, with an incidence higher in Black than in non-Black patients. Angioedema associated with laryngeal edema may be fatal. If angioedema of the face, extremities, lips, tongue, glottis and/or larynx occurs, treatment with lisinopril and hydrochlorothiazide should be discontinued and appropriate therapy instituted immediately. In rare cases, intestinal angioedema has been reported with angiotensin converting enzyme inhibitors including lisinopril. (See WARNINGS.)
Hypotension: In clinical trials, adverse effects relating to hypotension occurred as follows: hypotension (1.4), orthostatic hypotension (0.5), other orthostatic effects (3.2). In addition syncope occurred in 0.8 percent of patients. (See WARNINGS.)
Cough: See PRECAUTIONS, Cough.

Clinical Laboratory Test Findings

Serum Electrolytes: See PRECAUTIONS.
Creatinine, Blood Urea Nitrogen: Minor reversible increases in blood urea nitrogen and serum creatinine were observed in patients with essential hypertension treated with lisinopril and hydrochlorothiazide. More marked increases have also been reported and were more likely to occur in patients with renal artery stenosis. (See PRECAUTIONS.)
Serum Uric Acid, Glucose, Magnesium, Cholesterol, Triglycerides and Calcium: See PRECAUTIONS.

OVERDOSAGE

No specific information is available on the treatment of overdosage with lisinopril and hydrochlorothiazide. Treatment is symptomatic and supportive. Therapy with lisinopril and hydrochlorothiazide should be discontinued and the patient observed closely. Suggested measures include induction of emesis and/or gastric lavage, and correction of dehydration, electrolyte imbalance and hypotension by established procedures.

Lisinopril

Following a single oral dose of 20 mg/kg, no lethality occurred in rats and death occurred in one of 20 mice receiving the same dose. The most likely manifestation of overdosage would be hypotension, for which the usual treatment would be intravenous infusion of normal saline solution.
Lisinopril can be removed by hemodialysis. (See WARNINGS, Anaphylactoid reactions during membrane exposure.)

Hydrochlorothiazide

Oral administration of a single oral dose of 10 mg/kg to mice and rats was not lethal. The most common signs and symptoms observed are those caused by electrolyte depletion (hypokalemia, hypochloremia, hyponatremia) and dehydration resulting from excessive diuresis. If digitalis has also been administered, hypokalemia may accentuate cardiac arrhythmias.

DOSAGE AND ADMINISTRATION

Lisinopril is an effective treatment of hypertension in once-daily doses of 10 to 80 mg, while hydrochlorothiazide is effective in doses of 12.5 to 50 mg. In clinical trials of lisinopril/hydrochlorothiazide combination therapy using lisinopril doses of 10 to 80 mg and hydrochlorothiazide doses of 6.25 to 50 mg, the antihypertensive response rates generally increased with increasing dose of either component.
The side effects (see WARNINGS) of lisinopril are generally rare and apparently independent of dose; those of hydrochlorothiazide are a mixture of dose-dependent phenomena (primarily hypokalemia) and dose-independent phenomena (e.g., pancreatitis), the former much more common than the latter. Therapy with any combination of lisinopril and hydrochlorothiazide will be associated with both sets of dose-independent side effects, but addition of lisinopril in clinical trials blunted the hypokalemia normally seen with diuretics.
To minimize dose-independent side effects, it is usually appropriate to begin combination therapy only after a patient has failed to achieve the desired effect with monotherapy.

Dose Titration Guided by Clinical Effect

A patient whose blood pressure is not adequately controlled with either lisinopril or hydrochlorothiazide monotherapy may be switched to lisinopril and hydrochlorothiazide tablets 10 mg/12.5 mg or lisinopril and hydrochlorothiazide tablets 20 mg/12.5 mg. Further increases of either or both components could depend on clinical response. The hydrochlorothiazide dose should generally not be increased until 2-3 weeks have elapsed. Patients whose blood pressures are adequately controlled with 25 mg of daily hydrochlorothiazide, but who experience significant potassium loss with this regimen, may achieve similar or greater blood pressure control with less potassium loss if they are switched to lisinopril and hydrochlorothiazide tablets 10 mg/12.5 mg. Dosage higher than lisinopril 80 mg and hydrochlorothiazide 50 mg should not be used.

Replacement Therapy

The combination may be substituted for the titrated individual components.

Use in Renal Impairment

The usual regimens of therapy with lisinopril and hydrochlorothiazide tablets need not be adjusted as long as the patient's creatinine clearance is >30 mL/min/1.73 m2 (serum creatinine approximately (3 mg/dL or 265 µmol/L). In patients with more severe renal impairment, loop diuretics are preferred to thiazides, so lisinopril and hydrochlorothiazide tablets are not recommended (see WARNINGS, Anaphylactoid reactions during membrane exposure).

HOW SUPPLIED

Lisinopril and Hydrochlorothiazide Tablets USP, 10 mg/12.5 mg are blue, hexagonal tablets, with "LL" debossed on one side and "B01" on other side.
They are supplied as follows:
NDC 68180-518-01 – 100’s bottle
NDC 68180-518-02 – 500’s bottle
Lisinopril and Hydrochlorothiazide Tablets USP, 20 mg/12.5 mg are yellow, round tablets, with "LL" debossed on one side and "B02" on other side.
They are supplied as follows:
NDC 68180-519-01 – 100’s bottle
NDC 68180-519-02 – 500’s bottle
Lisinopril and Hydrochlorothiazide Tablets USP, 20 mg/25 mg are peach, round tablets, with "LL" debossed on one side and "B03" on other side.
They are supplied as follows:
NDC 68180-520-01 – 100’s bottle
NDC 68180-520-02 – 500’s bottle
Storage
Store at 20° to 25°C (68° to 77°F). [See USP Controlled Room Temperature]. Protect from excessive light and humidity.

Manufactured for:
Lupin Pharmaceuticals, Inc.
Baltimore, Maryland 21202
United States

Manufactured by:
Lupin Limited
Goa 403 722
INDIA
Or
Lupin Limited
Pithampur (M.P.) 454 775
INDIA
Revised: 15th April 2011 ID#: 224651

PRINCIPAL DISPLAY PANEL

LISINOPRIL AND HYDROCHLOROTHIAZIDE TABLETS USP
Rx Only
10 mg/12.5 mg

NDC 66336-0572-XX

Tablets